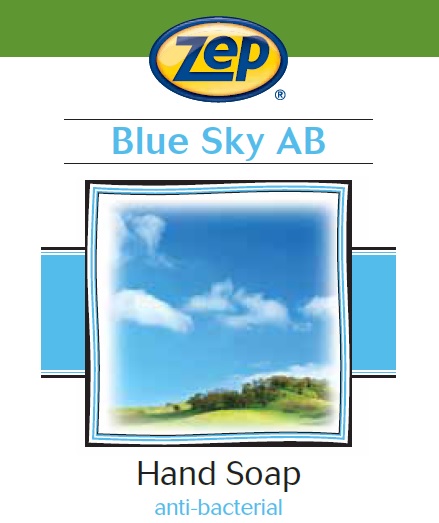 DRUG LABEL: Zep Blue Sky AB
NDC: 66949-124 | Form: LIQUID
Manufacturer: Zep Inc.
Category: otc | Type: HUMAN OTC DRUG LABEL
Date: 20251226

ACTIVE INGREDIENTS: BENZALKONIUM CHLORIDE 0.13 g/100 mL
INACTIVE INGREDIENTS: WATER; CETRIMONIUM CHLORIDE; LAUROYL/MYRISTOYL AMIDOPROPYL AMINE OXIDE; PHENOXYETHANOL; IODOPROPYNYL BUTYLCARBAMATE; METHYLISOTHIAZOLINONE; FD&C BLUE NO. 1; ANHYDROUS CITRIC ACID; GLYCERIN; DI-PPG-2 MYRETH-10 ADIPATE; HEXANEDIOL; TETRASODIUM IMINODISUCCINATE; METHYLCHLOROISOTHIAZOLINONE

66949-124 / 3321 Blue Sky AB Foam

Active Ingredient

Benzalkonium Chloride 0.13%

Purpose

Antiseptic Handwash

Uses

Hand washing to decrease bacteria on skin.

Warnings

For external use only.

Do not use in or around the eyes ; if in eyes, rinse promptly and thoroughly with water.

When using this product

- Do not swallow.
- If swallowed, give large quantities of water to drink and consult a physician immediately.

Stop use and ask a doctor if skin irritation or redness persists for more than 72 hours.

Keep out of reach of children except under adult supervision.

Directions

- Wet hands with water.
- Place hands under dispenser.
- Apply foamed soap.
- Massage soap into hands and wrists, emphasizing back of hands, knuckles, and cuticles.
- Rinse hands thoroughly and dry.

Other information

- Store at 20 to 25°C (68 to 77°F).
- Do not freeze.
- Dispose in accordance with all applicable federal, state and local regulations.

Inactive ingredients

Water, Cetrimonium Chloride, Lauryl/Myristyl Amidopropyl Amine Oxide, Glycerin, Di-PPG-2 Myreth-10 Adipate, Phenoxyethanol, Iodopropynyl Butylcarbamate, Methylisothiazolinone, Hexanediol, Tetrasodium Iminodisuccinate, Fragrance, Methylchloroisothiazolinone, Citric Acid, Blue 1

Questions or comments?

Call 1-877-I-BUY-ZEP (1-877-428-9937)